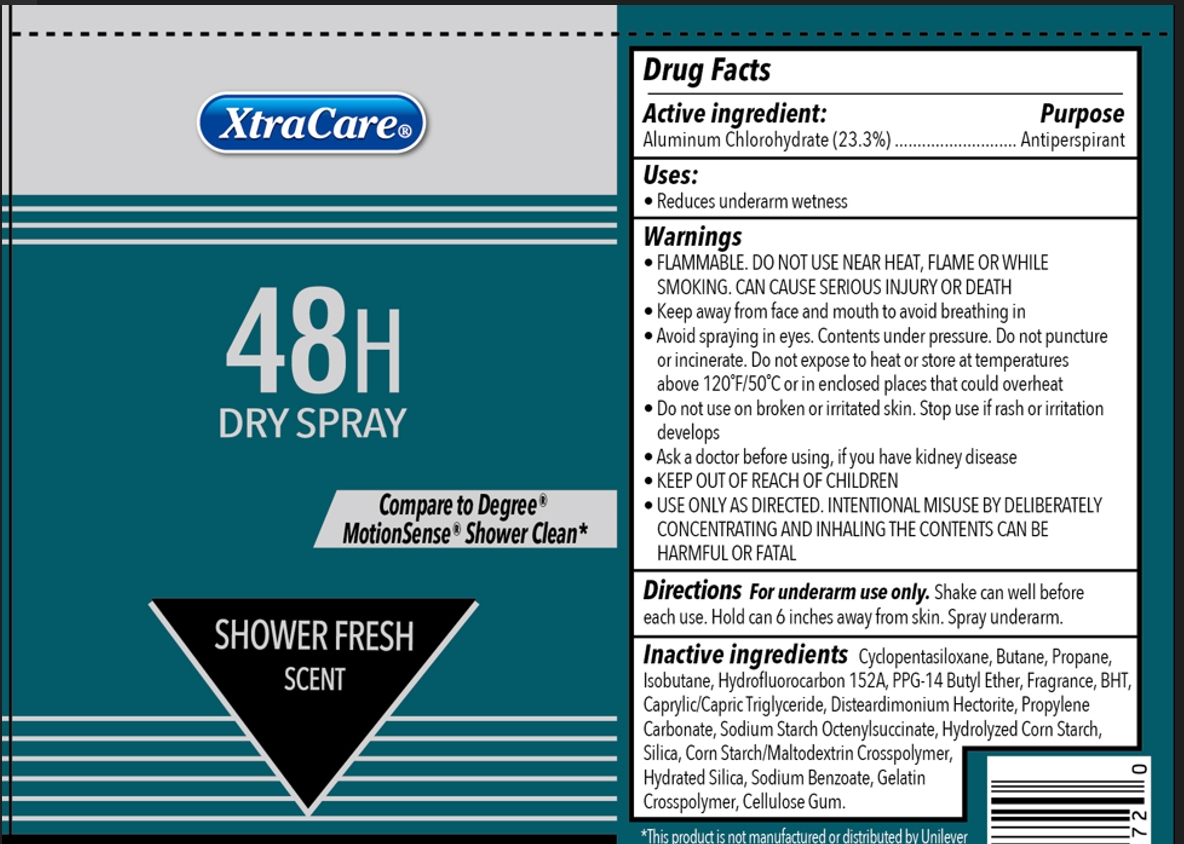 DRUG LABEL: Dry Shower Fresh 3.5oz
NDC: 57337-155 | Form: AEROSOL, SPRAY
Manufacturer: Rejoice International Corp.
Category: otc | Type: HUMAN OTC DRUG LABEL
Date: 20250206

ACTIVE INGREDIENTS: ALUMINUM CHLOROHYDRATE 23.3 g/100 g
INACTIVE INGREDIENTS: ALUMINUM STARCH OCTENYLSUCCINATE; GELATIN, UNSPECIFIED; PPG-14 BUTYL ETHER; BUTYLATED HYDROXYTOLUENE; SILICON DIOXIDE; 1,1-DIFLUOROETHANE; ISOBUTANE; HYDRATED SILICA; CORN SYRUP; STARCH, CORN; CYCLOMETHICONE 5; BUTANE; PROPANE; MEDIUM-CHAIN TRIGLYCERIDES; SODIUM BENZOATE; CARBOXYMETHYLCELLULOSE SODIUM, UNSPECIFIED FORM; PROPYLENE CARBONATE; DISTEARDIMONIUM HECTORITE

Dry Spray Shower Fresh 3.5oz

Active ingredient

Aluminum Chlorohydrate 23.3%

Purpose

Antiperspirant

Uses

Reduces underarm wetness

Warnings

Flammable. Do not use near heat, flame or while smoking. Can cause serious injury or death

Do not use on broken or irritated skin. Stop use if rash or irritation develops.

When using

- Keep away from face and mouth to avoid breathing in
- Avoid spraying in eyes. Contents under pressure. Do not puncture or incinerate. Do not expose to heat or store at temperatures above 120ºF/50ºC or enclosed places that could overheat.
- USE ONLY AS DIRECTED. INTENTIONAL MISUSE BY DELIBERATELY CONCENTRATING AND INHALING THE CONTENT CAN BE HARMFUL OR FATAL.

Ask a doctor before using, if you have kidney disease.

Keep out of reach of children

Directions

For underarm use only. Shake can well before each use. Hold can 6 inches away from skin. Spray underarm.

Inactive ingredients

Cyclopentasiloxane; Butane; Propane; Isobutane; Hydrofluorocarbon 152A; PPG-14 Butyl Ether; Fragrance; BHT; Caprylic/Capric Triglyceride; Disteardimonium Hectorite; Propylene Carbonate; Sodium Starch Octenylsuccinate; Hydrolyzed Corn Starch; Silica; Corn Starch/Maltodextrin Crosspolymer; Hydrated Silica; Sodium Benzoate; Gelatin Crosspolymer; Cellulose Gum